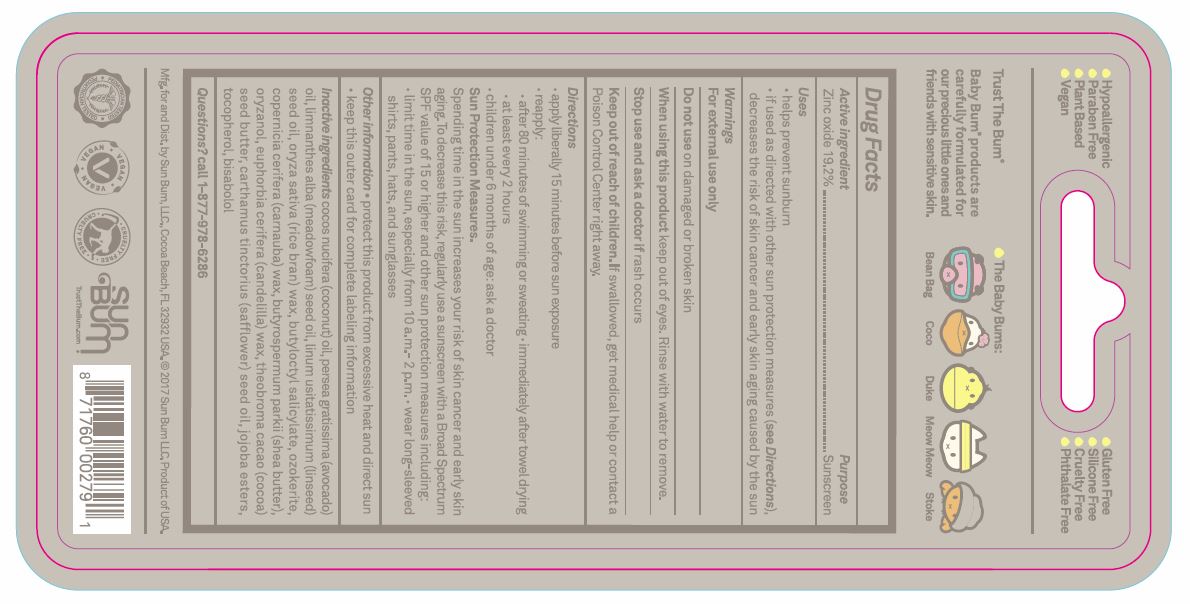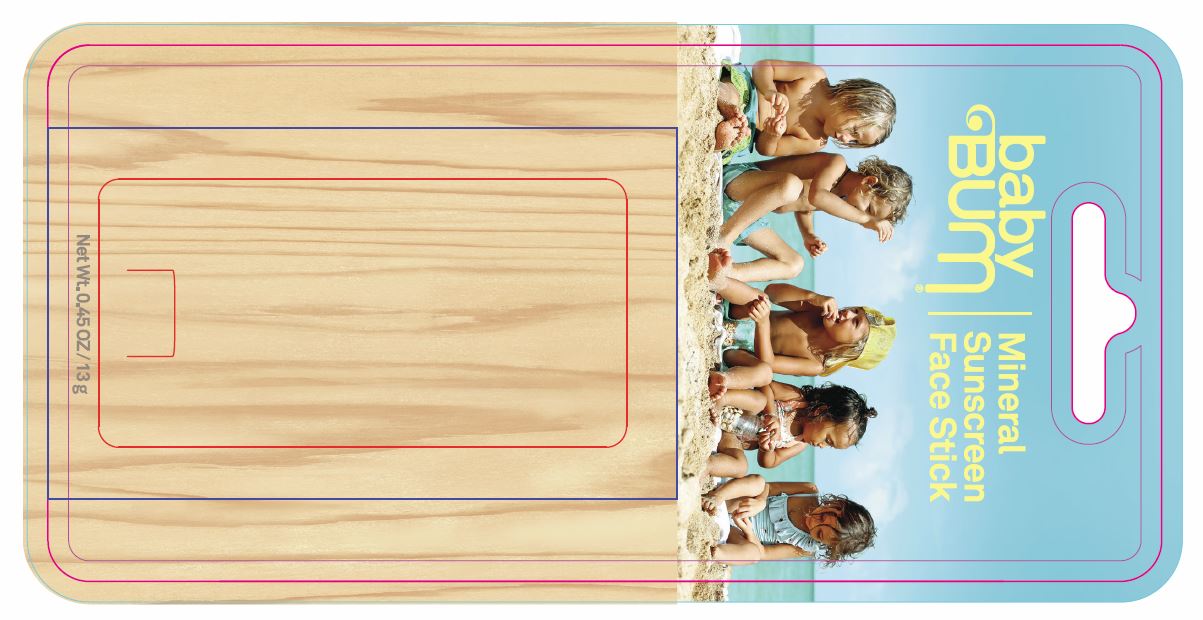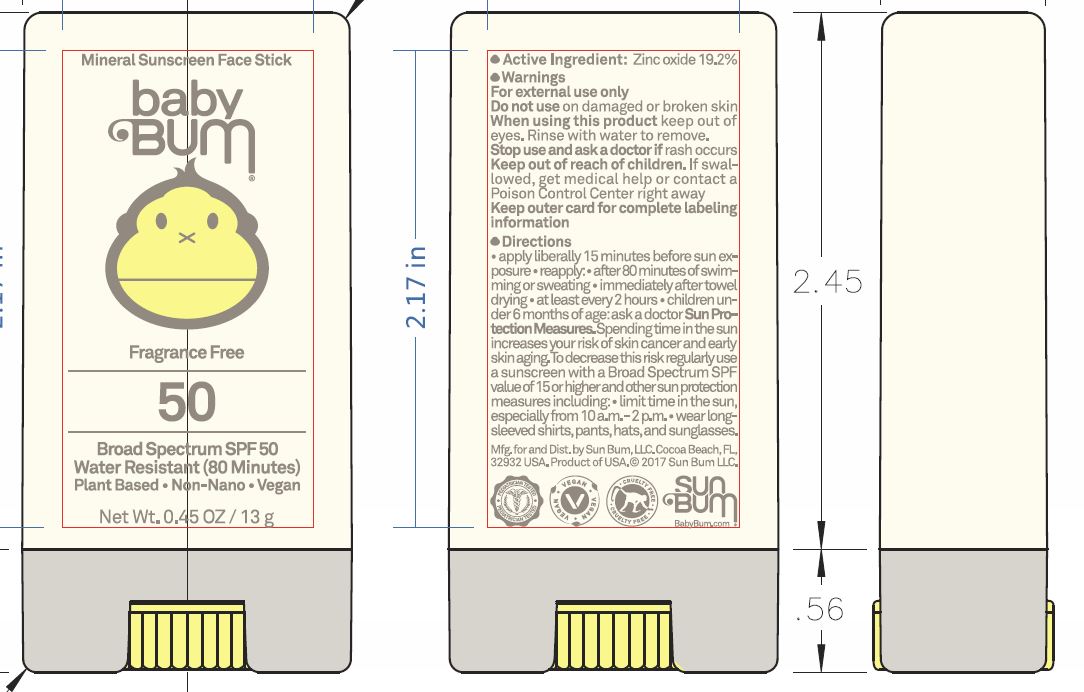 DRUG LABEL: Baby Bum Mineral SPF50 Sunscreen
NDC: 69039-271 | Form: STICK
Manufacturer: Sun Bum LLC
Category: otc | Type: HUMAN OTC DRUG LABEL
Date: 20220204

ACTIVE INGREDIENTS: ZINC OXIDE 192 mg/1 g
INACTIVE INGREDIENTS: COCONUT OIL; AVOCADO OIL; MEADOWFOAM SEED OIL; LINSEED OIL; RICE BRAN; CANDELILLA WAX; BUTYLOCTYL SALICYLATE; CARNAUBA WAX; CERESIN; SHEA BUTTER; GAMMA ORYZANOL; COCOA BUTTER; SAFFLOWER OIL; TOCOPHEROL; LEVOMENOL

Baby Bum Mineral SPF50 Sunscreen Face Stick

Active ingredient

Zinc oxide 19.2%

Purpose

Sunscreen

Uses

• helps prevent sunburn • if used as directed with other sun protection measures (see Directions), decreases the risk of skin cancer and early skin aging caused by the sun

Warnings

For external use only

Do not use

damaged or broken skin

When using this product

keep out of eyes. Rinse with water to remove.

Stop use and ask a doctor

if rash occurs

Keep out of reach of children.

If swallowed, get medical help or contact a Poison Control Center right away.

Directions

• apply liberally 15 minutes before sun exposure reapply: • after 80 minutes of swimming or sweating • immediately after towel drying • at least every 2 hours • children under 6 months of age: ask a doctor Sun Protection Measures. Spending time in the sun increases your risk of skin cancer and early skin aging. To decrease this risk, regularly use a sunscreen with a Broad Spectrum SPF value of 15 or higher and other sun protection measures including: • limit time in the sun, especially from 10 a.m.-2 p.m. • wear long-sleeved shirts, pants, hats, and sunglasses

Other information

• protect this product from excessive heat and direct sun • keep this outer card for complete labeling information

Inactive ingredients

cocos nucifera (coconut) oil, persea gratissima (avocado) oil, limnanthes alba (meadowfoam) seed oil, linum usitatissimum (linseed) seed oil, oryza sativa (rice bran) wax, euphorbia cerifera (candelilla) wax, butyloctyl salicylate, copernicia cerifera (carnauba) wax, ozokerite, butyrospermum parkii (shea butter), oryzanol, fragrance, theobroma cacao (cocoa) seed butter, carthamus tinctorius (safflower) seed oil, jojoba esters, tocopherol, bisabolol

Questions?

call 1-877-978-6286